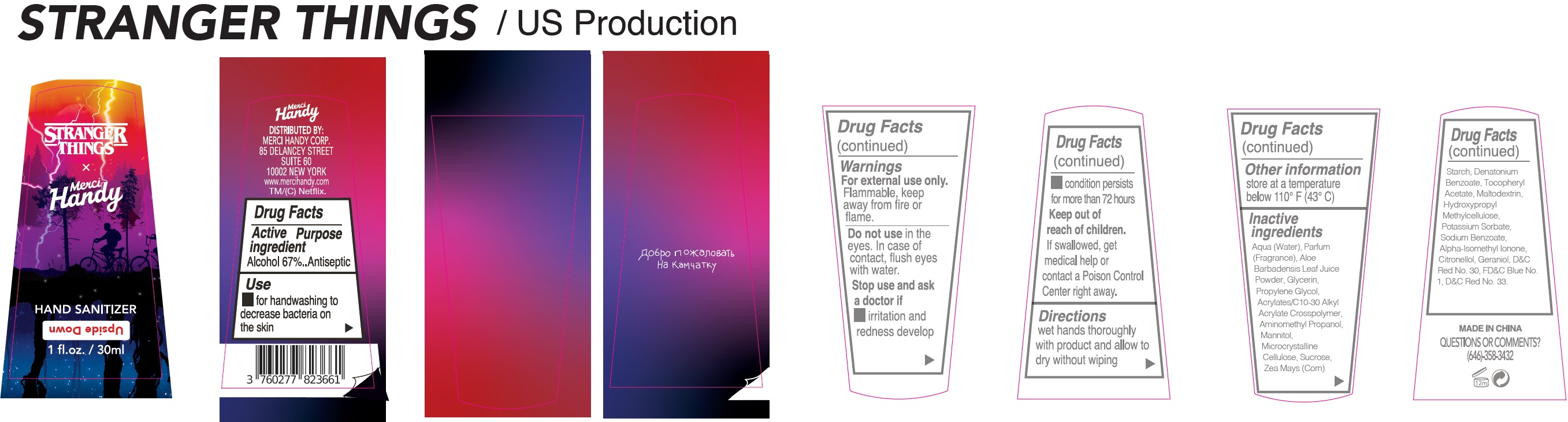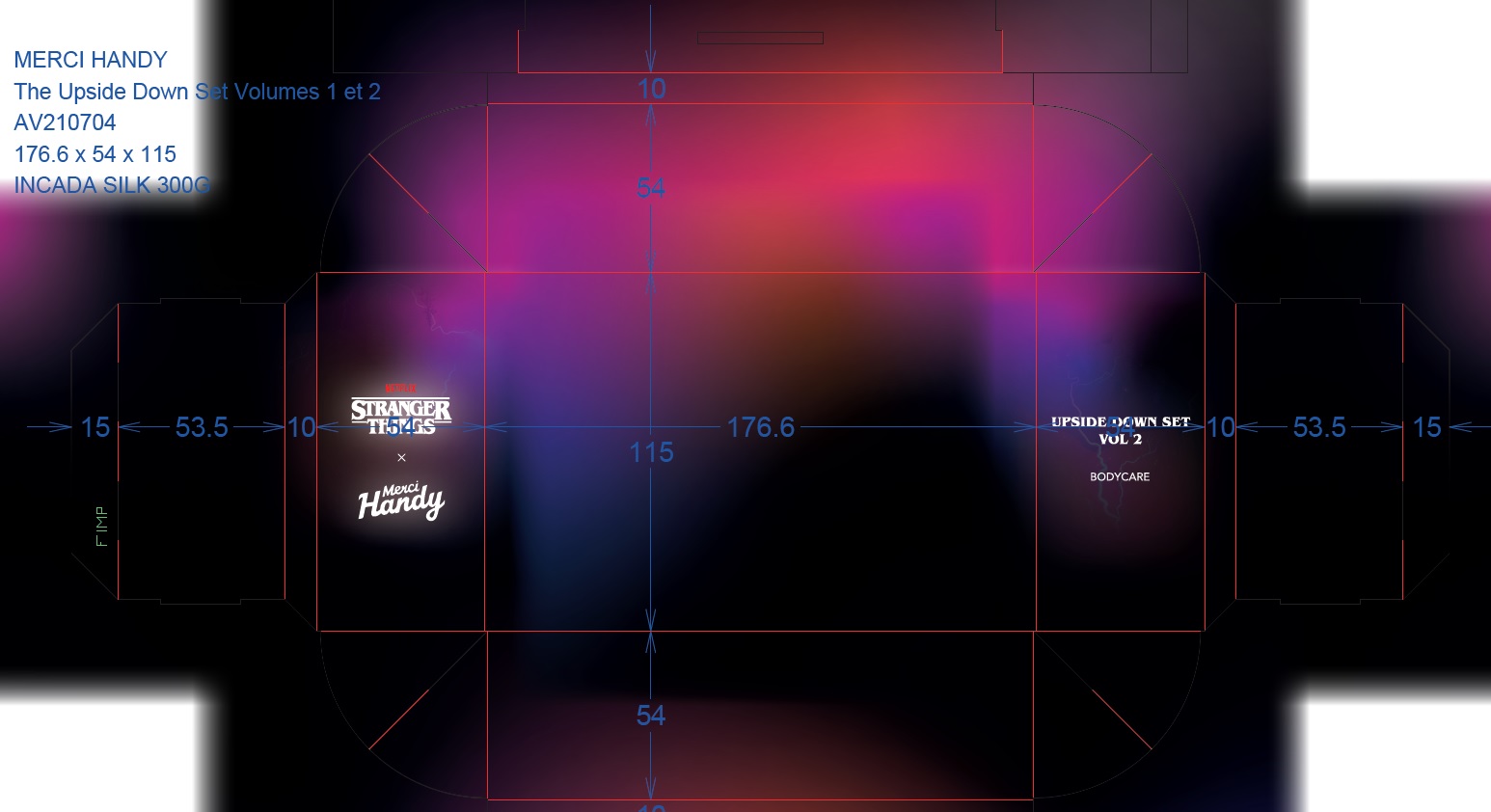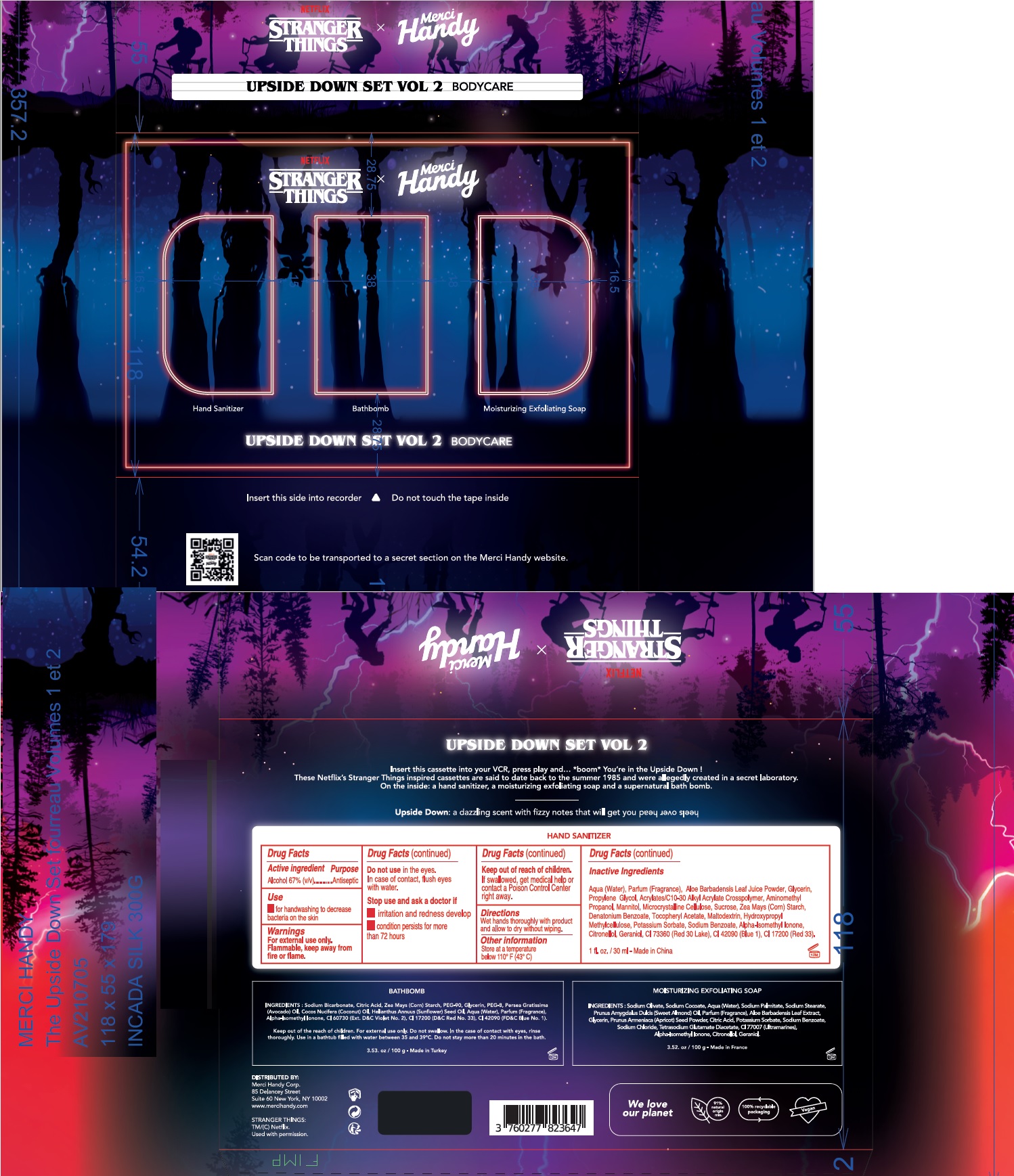 DRUG LABEL: Upside Down Set Vol 2 Bodycare
NDC: 72866-037 | Form: KIT | Route: TOPICAL
Manufacturer: MERCI HANDY CORPORATION
Category: otc | Type: HUMAN OTC DRUG LABEL
Date: 20240123

ACTIVE INGREDIENTS: ALCOHOL 67 mL/100 mL
INACTIVE INGREDIENTS: MALTODEXTRIN; HYPROMELLOSE, UNSPECIFIED; POTASSIUM SORBATE; SODIUM BENZOATE; ISOMETHYL-.ALPHA.-IONONE; .BETA.-CITRONELLOL, (R)-; GERANIOL; D&C RED NO. 30; FD&C BLUE NO. 1; WATER; ALOE VERA LEAF; GLYCERIN; PROPYLENE GLYCOL; CARBOMER INTERPOLYMER TYPE A (ALLYL SUCROSE CROSSLINKED); AMINOMETHYLPROPANOL; MANNITOL; MICROCRYSTALLINE CELLULOSE; SUCROSE; CORN; DENATONIUM BENZOATE; .ALPHA.-TOCOPHEROL ACETATE

Upside Down Set Vol 2 Bodycare

Active ingredient

Alcohol 67% (v/v)

Purpose

Antiseptic

Use

- for handwashing to decrease bacteria on the skin

Warnings

For external use only. Flammable, keep away from fire or flame.

Do not use

in the eyes. In case of contact, flush eyes with water.

Stop use and ask a doctor if

- irritation and redness develop
- condition persists for more than 72 hours

Keep out of reach of children.

If swallowed, get medical help or contact a Poison Control Center right away.

Directions

Wet hands thoroughly with product and allow to dry without wiping

Other information

Store at a temperature below 110° F (43° C)

Inactive ingredients

Aqua (Water), Parfum (Fragrance), Aloe Barbadensis Leaf Juice Powder, Glycerin, Propylene Glycol, Acrylates/C10-30 Alkyl Acrylate Crosspolymer, Aminomethyl Propanol, Mannitol, Microcrystalline Cellulose, Sucrose, Zea Mays (Corn) Starch, Denatonium Benzoate, Tocopheryl Acetate, Maltodextrin, Hydroxypropyl Methylcellulose, Potassium Sorbate, Sodium Benzoate, Alpha-Isomethyl Ionone, Citronellol, Geraniol, CI 73360 (Red 30 Lake), CI 42090 (Blue 1), CI 17200 (Red 33).